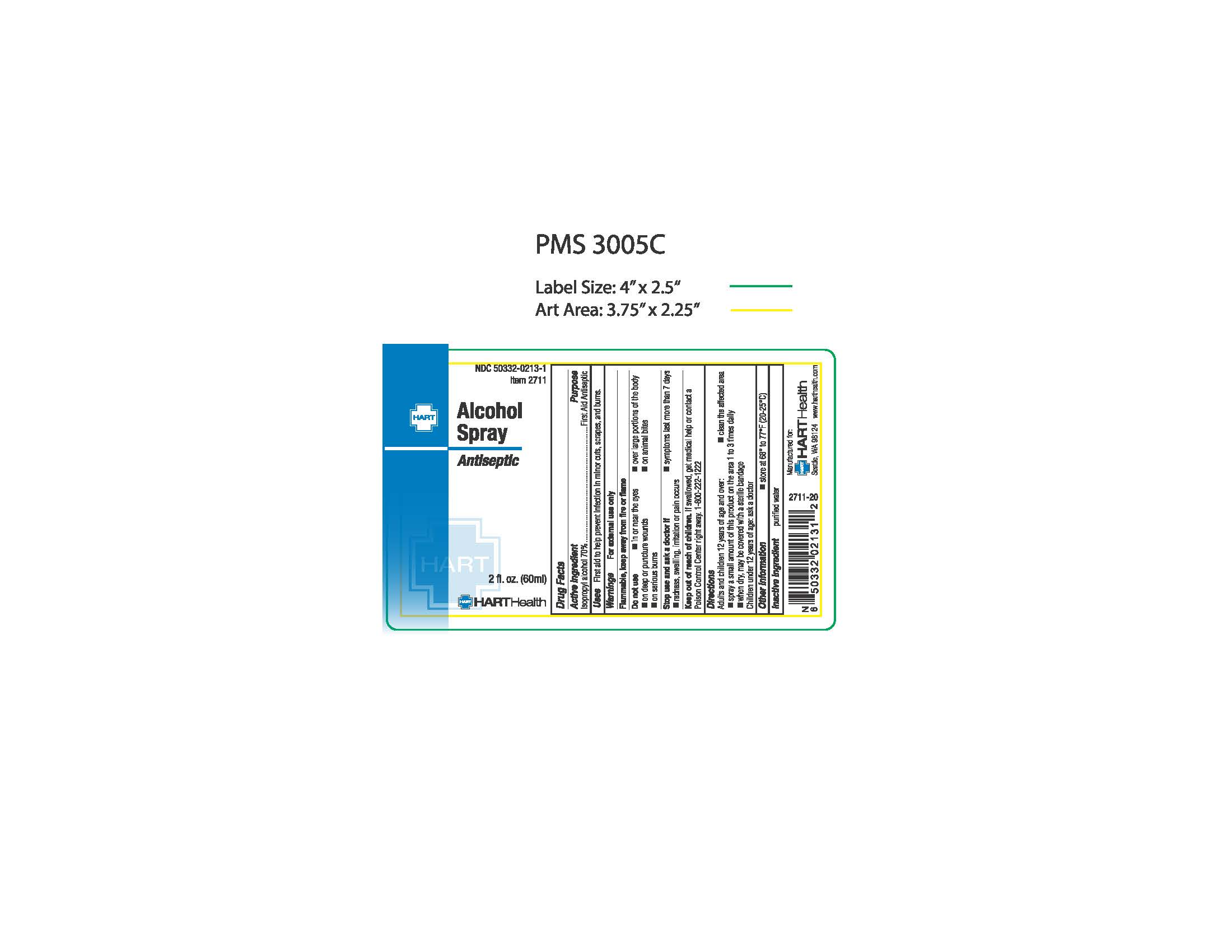 DRUG LABEL: Alcohol
NDC: 50332-0213 | Form: SPRAY
Manufacturer: NorMed
Category: otc | Type: HUMAN OTC DRUG LABEL
Date: 20240124

ACTIVE INGREDIENTS: ISOPROPYL ALCOHOL 70 mL/100 mL
INACTIVE INGREDIENTS: WATER

Isopropyl Alcohol Spray

Active Ingredient:

Isopropyl Alcohol 70%

Purpose:

First aid antiseptic

Uses:

First aid to help prevent infection in minor cuts, scrapes, and burns

Warnings

For external use only

Flammable, keep away from fire or flames

Do not use

- in the eyes
- over large portions of the body
- on deep or puncture wounds
- on animal bites
- on serious burns

Stop use and ask a doctor if

- the condition worsens
- the condition lasts for more than 7 days

Keep out of reach of children.

If swallowed, get medical help or contact a Poison Control Center right away. 1-800-222-1222

Directions:

Adults and children 2 years of age and over: apply topically to clean the affected area not more than 3 times daly

Children under 2 years of age: ask a doctor

Inactive ingredient

Purified Water